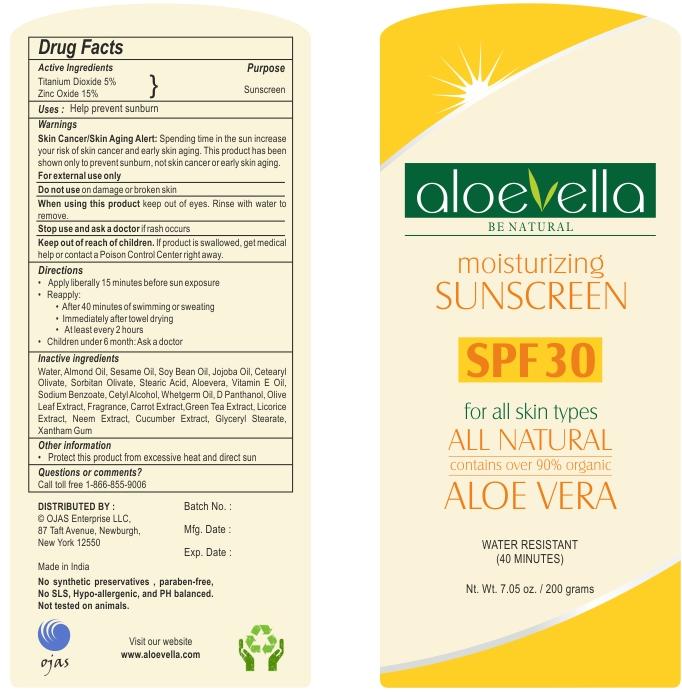 DRUG LABEL: aloevella
NDC: 55115-2041 | Form: CREAM
Manufacturer: Ojas Enterprises LLC
Category: otc | Type: HUMAN OTC DRUG LABEL
Date: 20111228

ACTIVE INGREDIENTS: TITANIUM DIOXIDE 5 g/100 g; ZINC OXIDE 15 g/100 g
INACTIVE INGREDIENTS: WATER; ALMOND OIL; SESAME OIL; SOYBEAN OIL; JOJOBA OIL; CETEARYL OLIVATE; SORBITAN OLIVATE; STEARIC ACID; ALOE VERA LEAF; ALPHA-TOCOPHEROL; SODIUM BENZOATE; CETYL ALCOHOL; WHEAT GERM OIL; DEXPANTHENOL; OLEA EUROPAEA LEAF; CARROT; GREEN TEA LEAF; LICORICE; AZADIRACHTA INDICA FLOWER; CUCUMBER; GLYCERYL MONOSTEARATE; XANTHAN GUM

Drug Facts

Active ingredients

Titanium dioxide 5%

Zinc Oxide 15%

purpose

Sunscreen

Uses

• Helps prevent sunburn

Warnings:

Skin Cancer/Skin Aging Alert: Spending time in the sun increase

your risk of skin cancer and early skin aging.This product has been

shown only to prevent sunburn,not skin cancer or early skin aging

For external use only

Do not use on damaged or broken skin

When using this product keep out of eyes. Rinse with water to remove.

Stop use and ask a doctor if rash occurs

Keep out of reach of children. If product is swallowed, get medical

help or contact a Poison Control Center right away.

Directions

• apply liberally 15 minutes before sun exposure

• reapply:

• after 40 minutes of swimming or sweating

• immediately after towel drying

• at least every 2 hours

• children under 6 months: Ask a doctor

Inactive ingredients

water, Almond oil, Sesame oil, Soy bean oil, Jojoba oil, Cetearyl olivate, sorbitan olivate, Stearic acid,

Aloevera, Vitamin E oil, Sodium Benzoate, Cetyl Alcohol, Whetgerm oil, D Panthanol, Olive leaf extract,

fragrance, Carrot extract, Green tea extract, Licorice extract, Neem extract, Cucumber extract, Glyceryl

stearate, Xanthan gum

Other information

• protect this product from excessive heat and direct sun

Questions or comments?

Call toll free 1-866-855-9006